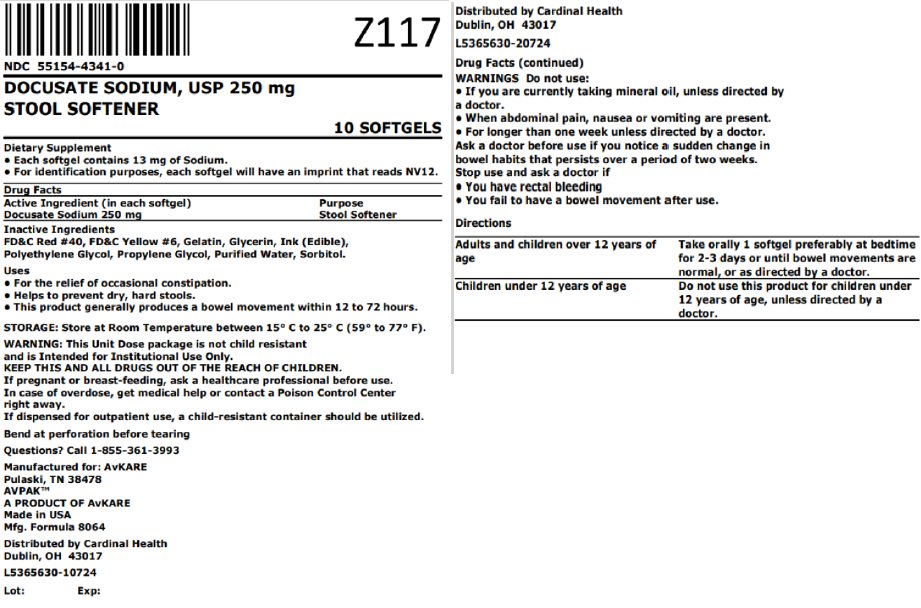 DRUG LABEL: Docusate Sodium
NDC: 55154-4341 | Form: CAPSULE, LIQUID FILLED
Manufacturer: Cardinal Health 107, LLC
Category: otc | Type: HUMAN OTC DRUG LABEL
Date: 20250822

ACTIVE INGREDIENTS: DOCUSATE SODIUM 250 mg/1 1
INACTIVE INGREDIENTS: FD&C RED NO. 40; FD&C YELLOW NO. 6; GELATIN, UNSPECIFIED; GLYCERIN; POLYETHYLENE GLYCOL 1000; PROPYLENE GLYCOL; WATER; SORBITOL

Docusate Sodium, USP
Stool Softener

Active ingredient (in each softgel)

Docusate Sodium 250 mg

Purpose

Stool Softener

Keep Out of Reach of Children.

In case of overdose, get medical help or contact a Poison Control Center right away.

Uses

- For the relief of occasional constipation.
- Helps to prevent dry, hard stools.
- This product generally produces a bowel movement within 12 to 72 hours.

Warnings

Do not use:

- If you are currently taking mineral oil, unless directed by a doctor.
- When abdominal pain, nausea, or vomiting are present.
- For longer than one week unless directed by a doctor.

Ask a doctor before use

if you notice a sudden change in bowel habits that persists over a period of two weeks.

Stop use and ask a doctor

if you have rectal bleeding or you fail to have a bowel movement after use.

If you are pregnant or breast-feeding,

ask a healthcare professional before use.

Directions

Adults and Children over 12 years of age | Take orally 1 softgel preferably at bedtime for 2-3 days or until bowel movements are normal, or as directed by a doctor.
Children under 12 years of age | Do not use this product for children under 12 years of age, unless directed by a doctor.

Other Information

- Each softgel contains 13 mg of Sodium.
- Store at room temperature between 15°C to 30°C (59°F to 86°F).
- Do not use if printed seal under cap is broken or missing.
- For identification purposes, each softgel will have an imprint that reads NV12.

Inactive ingredients

FD&C Red #40, FD&C Yellow #6, Gelatin, Glycerin, Ink (Edible), Polyethylene Glycol, Propylene Glycol, Purified Water, Sorbitol

Questions

Call 1-855-361-3993

.

Overbagged with 10 softgels per bag, NDC 55154-4341-0

WARNING: This Unit Dose package is not child resistant and is Intended for Institutional Use Only. Keep this and all drugs out of the reach of children.

Manufactured for:

AvKARE, Inc.

Pulaski, TN 38478

USA

Distributed By:

Cardinal Health

Dublin, OH 43017

L5365630-10724 / L5365630-20724

AV Rev. 05/16 (P)

Principal Display Panel

NDC 55154-4341-0

DOCUSATE SODIUM, USP 250 mg

STOOL SOFTENER

10 SOFTGELS